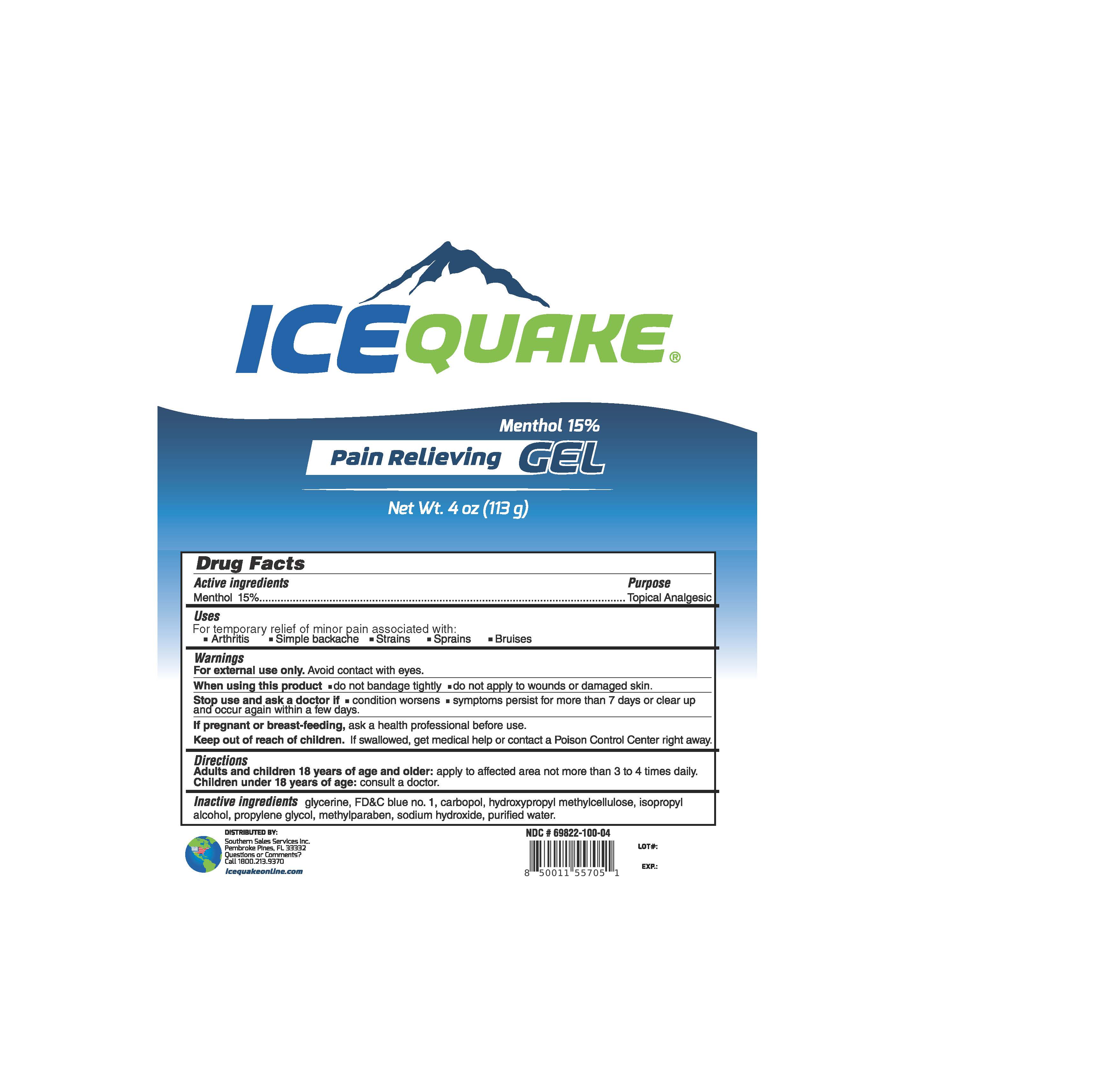 DRUG LABEL: Ice Quake
NDC: 69822-100 | Form: GEL
Manufacturer: Southern Sales & Service, Inc.
Category: otc | Type: HUMAN OTC DRUG LABEL
Date: 20231129

ACTIVE INGREDIENTS: MENTHOL 0.15 g/1 g
INACTIVE INGREDIENTS: GLYCERIN; FD&C BLUE NO. 1; CARBOMER HOMOPOLYMER, UNSPECIFIED TYPE; HYPROMELLOSE, UNSPECIFIED; ISOPROPYL ALCOHOL; PROPYLENE GLYCOL; METHYLPARABEN; SODIUM HYDROXIDE; WATER

IceQuake Pain Relieving

Drug Facts

Active ingredients

Menthol 15%

Purpose

Topical Analgesic

Uses

For temporary relief of minor pain associated with:

- arthritis
- simple backache
- strains
- sprains
- bruises

Warnings

Avoid contact with eyes. For external use only.

When using this product

- do not bandage tightly
- do not apply to wounds or damaged skin.

Stop use and ask a doctor if

- condition worsens
- symptoms persist for more than 7 days or clear up and occur again within a few days.

If pregnant or breast-feeding,

ask a health professional before use.

Keep out of the reach of children.

If swallowed, get medical help or contact a Poison Control Center right away.

Directions

apply to affected area not more than 3 to 4 tmes daily. Adults and children 18 years of age and older:

consult a doctor. Children under 18 years of age:

Inactive ingredients

glycerine, FD&C blue no. 1, carbopol, hydroxypropyl methylcellulose, isopropyl alcohol, propylene glycol, methylparaben, sodium hydroxide, purified water.